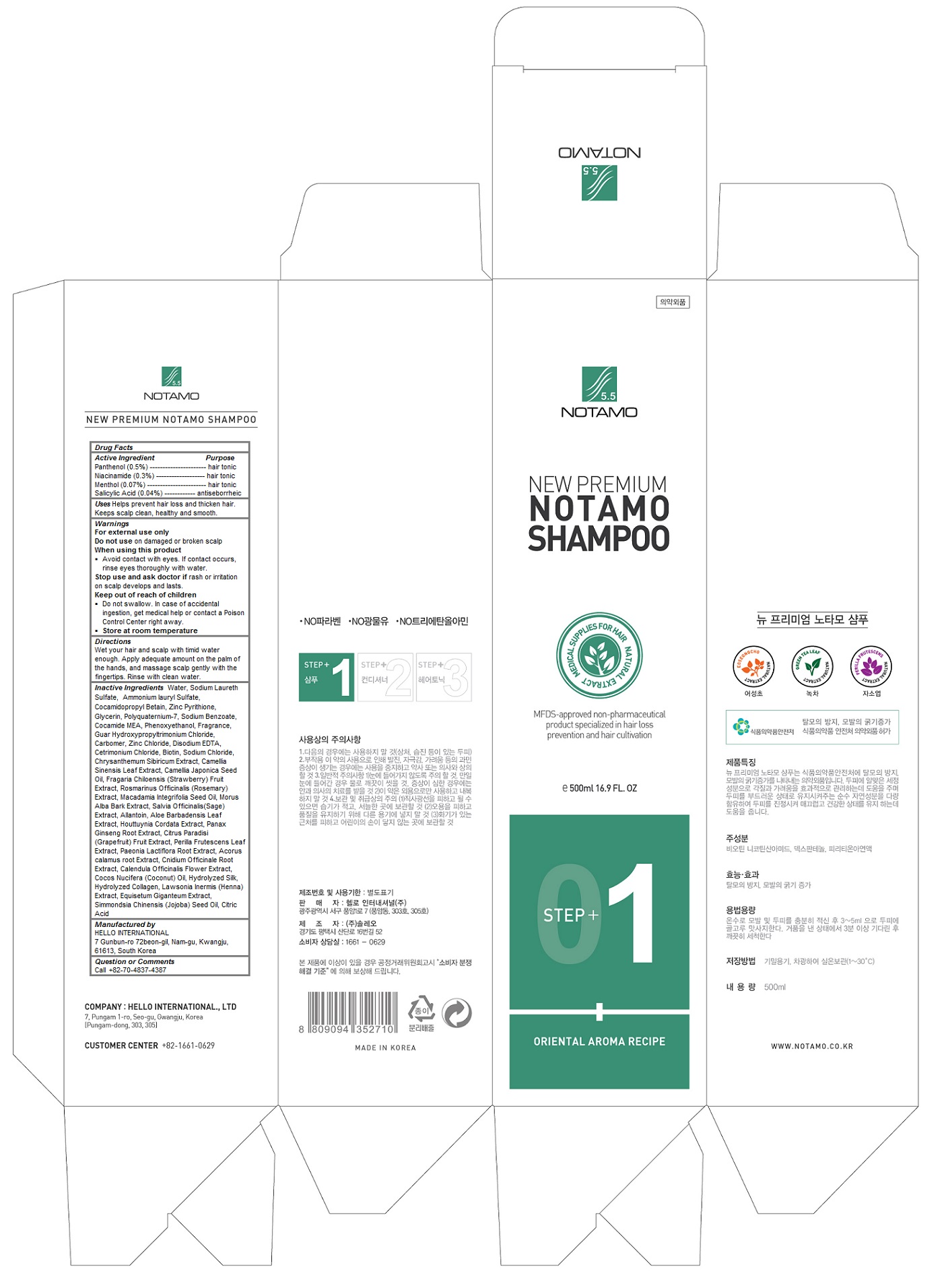 DRUG LABEL: New Premium Notamo
NDC: 69709-105 | Form: SHAMPOO
Manufacturer: HELLO INTERNATIONAL
Category: otc | Type: HUMAN OTC DRUG LABEL
Date: 20160427

ACTIVE INGREDIENTS: Panthenol 0.005 1/500 mL; Niacinamide 0.003 1/500 mL; Menthol 0.0007 1/500 mL; Salicylic Acid 0.0004 1/500 mL
INACTIVE INGREDIENTS: water; Sodium Laureth Sulfate; Ammonium Lauryl Sulfate; Cocamidopropyl Betaine; PYRITHIONE ZINC; Glycerin; POLYQUATERNIUM-7 (70/30 ACRYLAMIDE/DADMAC; 1600000 MW); Sodium Benzoate; COCO MONOETHANOLAMIDE; Phenoxyethanol; GUAR HYDROXYPROPYLTRIMONIUM CHLORIDE (1.7 SUBSTITUENTS PER SACCHARIDE); CARBOXYPOLYMETHYLENE; Zinc Chloride; EDETATE DISODIUM; Cetrimonium Chloride; Biotin; Sodium Chloride; GREEN TEA LEAF; Camellia Japonica Seed Oil; BEACH STRAWBERRY; ROSEMARY; MACADAMIA OIL; MORUS ALBA BARK; SALVIA OFFICINALIS ROOT; Allantoin; ALOE VERA LEAF; HOUTTUYNIA CORDATA FLOWERING TOP; ASIAN GINSENG; GRAPEFRUIT; PERILLA FRUTESCENS TOP; PAEONIA LACTIFLORA ROOT; ACORUS CALAMUS ROOT; CNIDIUM OFFICINALE ROOT; CALENDULA OFFICINALIS FLOWEr; COCONUT OIL; JOJOBA OIL; CITRIC ACID MONOHYDRATE

New Premium Notamo Shampoo